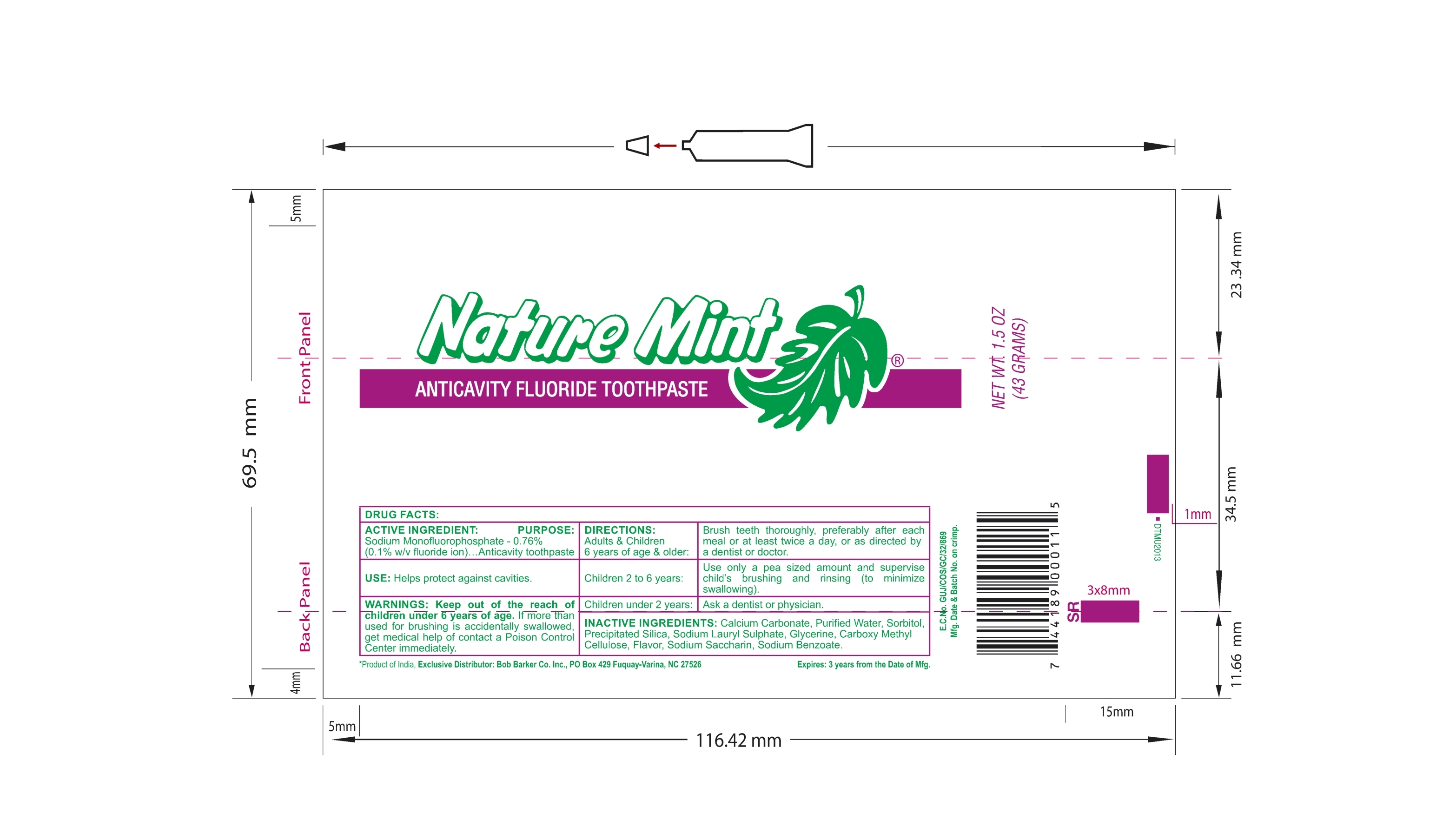 DRUG LABEL: Nature Mint Anticavity
NDC: 76001-001 | Form: PASTE, DENTIFRICE
Manufacturer: Daxal Cosmetics Private Limited
Category: otc | Type: HUMAN OTC DRUG LABEL
Date: 20190813

ACTIVE INGREDIENTS: SODIUM MONOFLUOROPHOSPHATE 0.76 g/100 g
INACTIVE INGREDIENTS: GLYCERIN; CALCIUM CARBONATE; WATER; SORBITOL; SILICON DIOXIDE; SODIUM LAURYL SULFATE; CARBOXYMETHYLCELLULOSE SODIUM, UNSPECIFIED FORM; SACCHARIN SODIUM; SODIUM BENZOATE

Nature Mint Anticavity

ACTIVE INGREDIENT

Sodium Monofluorophosphate - 0.76% (Total Fluoride Content - 1000 ppm Approx.)

DRUG FACTS

PURPOSE

Anticavity.

USE

Helps protect against cavities.

WARNINGS

Keep out of reach of children under 6 years of age. If more than used for brushing is accidentally swallowed, get medical help or contact a Poison Control Center immediately.

INACTIVE INGREDIENTS

Calcium Carbonate, Purified Water, Sorbitol, Precipitated Silica, Sodium Lauryl Sulphate, Glycerin, Sodium Carboxy Methyl Cellulose, Flavor, Sodium Saccharin, Sodium Benzoate.

DIRECTIONS:

Adults & Children 6 years of age & older : Brush teeth throughly, preferably after each meal or at least twice a day, or as directed by a dentist or doctor.

Children 2 to 6 years : Use only a pea sized amount and supervise child's brushing and rinsing (to minimize swallowing).

Children under 2 years : Ask a dentist or physician.